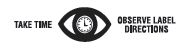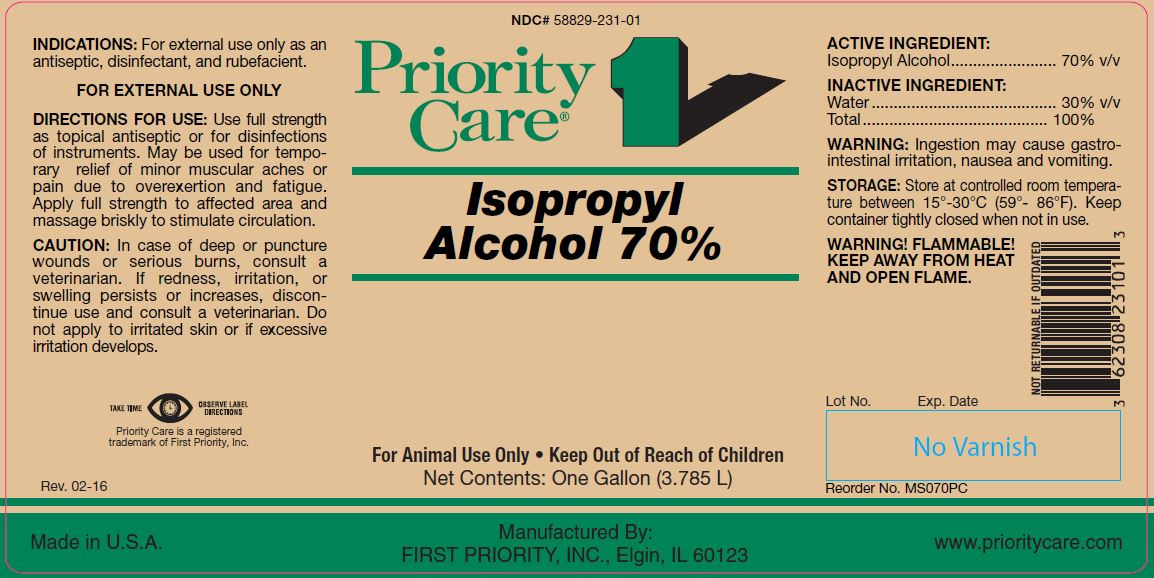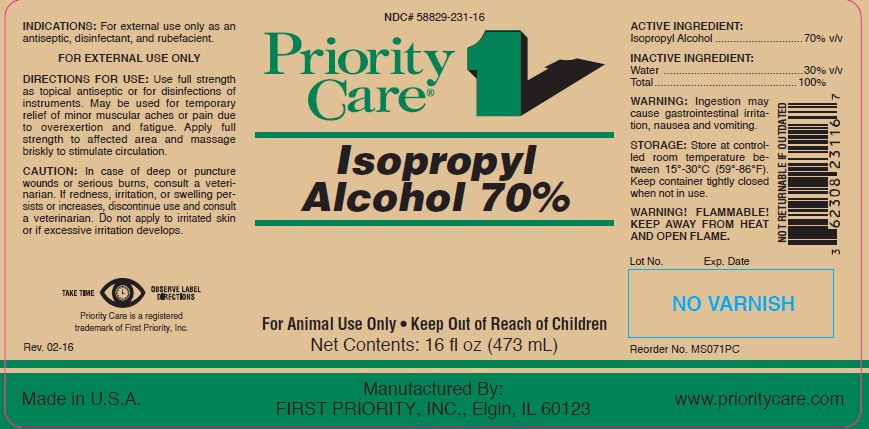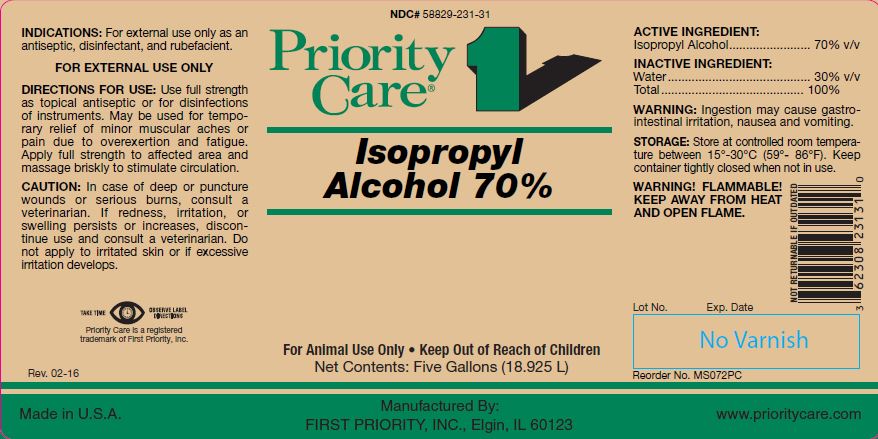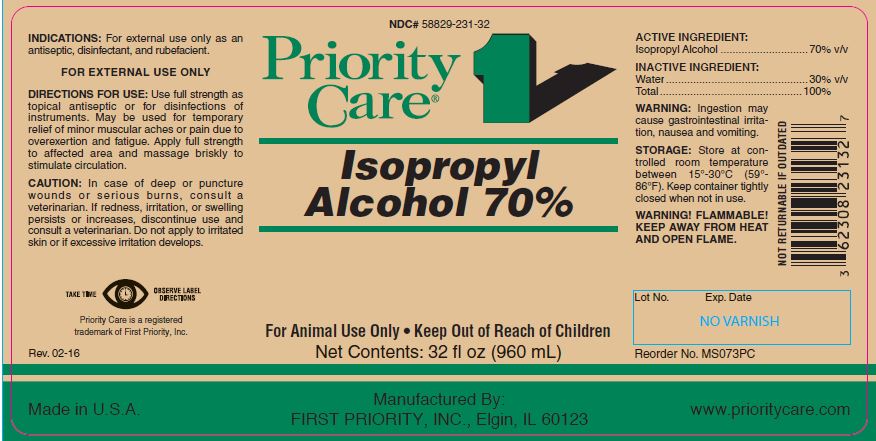 DRUG LABEL: Isopropyl Alcohol
NDC: 58829-231 | Form: LIQUID
Manufacturer: FIRST PRIORITY INCORPORATED
Category: animal | Type: OTC ANIMAL DRUG LABEL
Date: 20241029

ACTIVE INGREDIENTS: ISOPROPYL ALCOHOL 557.25 g/1 L

Isopropyl Alcohol 70%

KEEP OUT OF REACH OF CHILDREN

For Animal Use Only
Keep Out of Reach of Children

HOW SUPPLIED

Net Contents: 16 fl oz (473 mL) Reorder No. MS071PC

Net Contents: 32 fl oz (960 mL) Reorder No. MS073PC

Net Contents: One Gallon (3.785 L) Reorder No. MS070PC

Net Contents: Five Gallons (18.925 L) Reorder No. MS072PC

INDICATIONS:

For external use only as an antiseptic, disinfectant, and rubefacient.

FOR EXTERNAL USE ONLY

DIRECTIONS FOR USE:

Use full strength as topical antiseptic or for disinfections of instruments. May be used for temporary relief of minor muscular aches or pain due to overexertion and fatigue. Apply full strength to affected area and massage briskly to stimulate circulation.

CAUTION:

In case of deep or puncture wounds or serious burns, consult a veterinarian. If redness, irritation, or swelling persists or increases, discontinue use and consult a veterinarian. Do not apply to irritated skin or if excessive irritation develops.

ACTIVE INGREDIENT:

Isopropyl Alcohol........................ 70% v/v

INACTIVE INGREDIENT:

Water .......................................... 30% v/v
Total .......................................... 100%

WARNING:

Ingestion may cause gastrointestinal irritation, nausea and vomiting.

STORAGE:

Store at controlled room temperature between 15°-30°C (59°- 86°F). Keep container tightly closed when not in use.

WARNINGS

WARNING! FLAMMABLE! KEEP AWAY FROM HEAT AND OPEN FLAME.

INFORMATION FOR OWNERS/CAREGIVERS

Priority Care is a registered trademark of First Priority, Inc.

Made in U.S.A.

Manufactured By: FIRST PRIORITY, INC., Elgin, IL 60123

www.prioritycare.com

NOT RETURNABLE IF OUTDATED